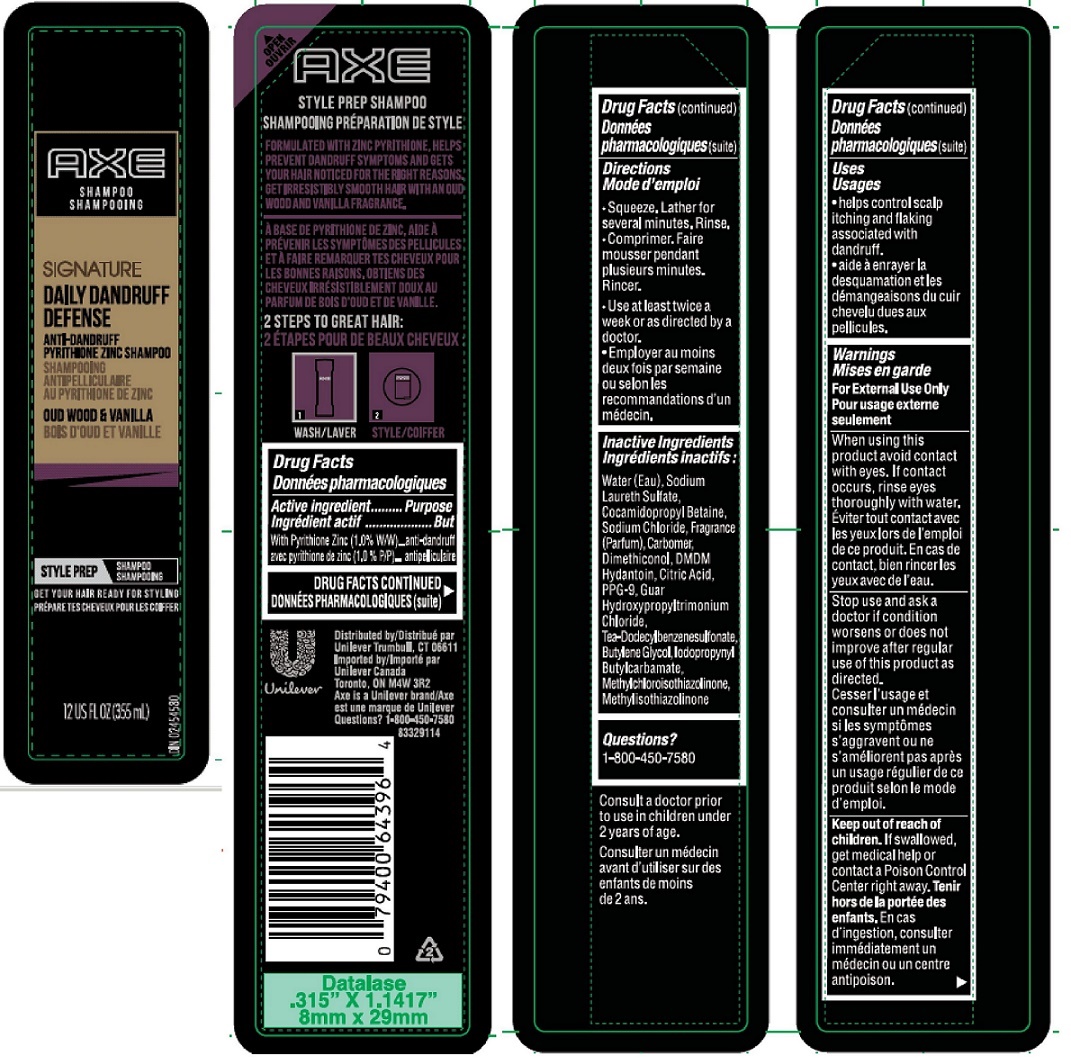 DRUG LABEL: Axe

NDC: 64942-1483 | Form: SHAMPOO
Manufacturer: Conopco, Inc. d/b/a Unilever
Category: otc | Type: HUMAN OTC DRUG LABEL
Date: 20221207

ACTIVE INGREDIENTS: PYRITHIONE ZINC 1 g/100 mL
INACTIVE INGREDIENTS: WATER; SODIUM LAURETH-3 SULFATE; COCAMIDOPROPYL BETAINE; SODIUM CHLORIDE; CARBOMER HOMOPOLYMER TYPE C (ALLYL PENTAERYTHRITOL CROSSLINKED); DIMETHICONOL (40 CST); DMDM HYDANTOIN; CITRIC ACID MONOHYDRATE; PPG-9; GUAR HYDROXYPROPYLTRIMONIUM CHLORIDE (1.7 SUBSTITUENTS PER SACCHARIDE); TRIETHANOLAMINE DODECYLBENZENESULFONATE; BUTYLENE GLYCOL; IODOPROPYNYL BUTYLCARBAMATE; METHYLCHLOROISOTHIAZOLINONE; METHYLISOTHIAZOLINONE

Axe Signature Daily Dandruff Defense Anti-Dandruff Shampoo

Active ingredient

With Pyrithione Zinc (1.0% WW)

Purpose

anti-dandruff

Uses

- helps control scalp itching and flaking associated with dandruff.

Warnings

For External Use Only

When using this product avoid contact with eyes. If contact occurs, rinse eyes thoroughly with water.

Stop use and ask a doctor if condition worsens or does not improve after regular use of this product as directed.

Keep out of reach of children. If swallowed, get medical help or contact a Poison Control Center right away.

Directions

- Squeeze. Lather for several minutes. Rinse.
- Use at least twice a week or as directed by a doctor.

Inactive Ingredients

Water, Sodium Laureth Sulfate, Cocamidopropyl Betaine, Sodium Chloride, Fragrance (Parfum), Carbomer, Dimethiconol, DMDM Hydantoin, Citric Acid, PPG-9, Guar Hydroxypropyltrimonium Chloride, TEA-Dodecylbenzenesulfonate, Butylene Glycol, Iodopropynyl Butylcarbamate, Methylchloroisothiazolinone, Methylisothiazolinone

Questions?

1-800-450-7580

Consult a doctor prior to use in children under 2 years of age.